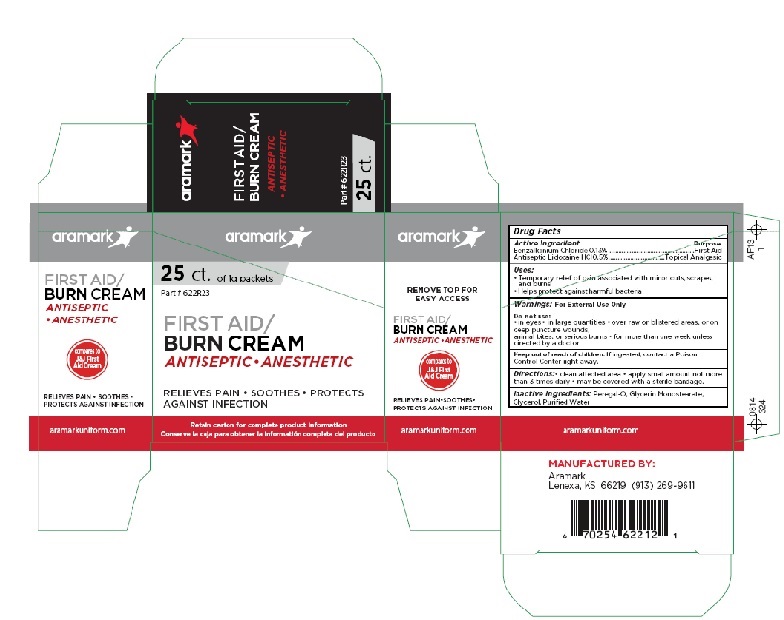 DRUG LABEL: Aramark Burn Cream
NDC: 81238-4622 | Form: CREAM
Manufacturer: Western First Aid Safety dba Aramark
Category: otc | Type: HUMAN OTC DRUG LABEL
Date: 20210521

ACTIVE INGREDIENTS: LIDOCAINE HYDROCHLORIDE 5 mg/1 g; BENZALKONIUM CHLORIDE 1.3 mg/1 g
INACTIVE INGREDIENTS: POLYOXYL 20 CETOSTEARYL ETHER; DIGLYCERIN MONOSTEARATE; GLYCERIN; WATER

aramark Burn Cream

Drug Facts

Active Ingredient
Benzalkonium Chloride 0.13%
Antiseptic Lidocaine HCI0.5%

Purpose
Benzalkonium Chloride ......First Aid Antiseptic

Lidocaine HCl .................Topical Analgesic

Uses:
• Temporary relief of pain associated with minor cuts, scrapes,
and burns
• Helps protect against harmful bacteria

Warnings: For External Use Only
Do not use:
• in eyes • in large quantities • over raw or blistered areas, or on
deep puncture wounds,
animal bites, or serious burns • for more than one week unless
directed by a doctor

Keep out of reach of children. If ingested, contact a Poison
Control Center right away.

Directions:
• clean affected area • apply small amount not more than 3 times
daily
• may be covered with a sterile bandage

Inactive Ingredients: Peregal-O, Glycerin Monostearate,
Glycerol, Purified Water

Product Package

aramark

25 ct. of 1g packets

FIRST AID/
BURN CREAM

ANTISEPTIC•ANESTHETIC

RELIEVES PAIN • SOOTHES • PROTECTS
AGAINST INFECTION

Retain carton for complete product information

REMOVE TOP FOR
EASY ACCESS

ANTISEPTIC•ANESTHETIC

compares to
J&J First
Aid Cream

RELIEVES PAIN•SOOTHES•
PROTECTS AGAINST INFECTION

aramarkuniform.com

MANUFACTURED BY:
Aramark
Lenexa, KS 66219 (913) 269-9611

res